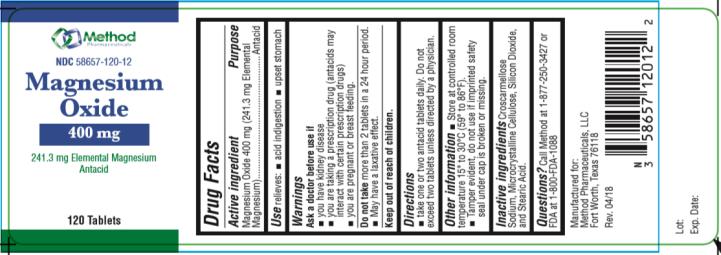 DRUG LABEL: Magnesium Oxide
NDC: 58657-120 | Form: TABLET
Manufacturer: Method Pharmaceuticals, LLC
Category: otc | Type: HUMAN OTC DRUG LABEL
Date: 20251021

ACTIVE INGREDIENTS: MAGNESIUM OXIDE 400 mg/1 1
INACTIVE INGREDIENTS: CROSCARMELLOSE SODIUM; CELLULOSE, MICROCRYSTALLINE; SILICON DIOXIDE; STEARIC ACID

Magnesium Oxide

Drug Facts

Active ingredient

Magnesium Oxide 400 mg

(241.3 mg Elemental Magnesium)

Purpose

Antacid

Use

relieves: ■ acid indigestion ■ upset stomach

Warnings

Ask a doctor before use if

- you have kidney disease
- you are taking a prescription drug (antacids may interact with certain prescription drugs)
- you are pregnant or breast feeding.

Do not take more than 2 tablets in a 24 hour period.

- May have a laxative effect.

Directions

- take one or two antacid tablets daily. Do not exceed two tablets unless directed by a physician.

Other information

- Store at controlled room temperature 15° to 30°C (59° to 86°F).
- Tamper evident, do not use if imprinted safety seal under cap is broken or missing.

Inactive ingredients

Croscarmellose Sodium, Microcrystalline Cellulose, Silicon Dioxide, and Stearic Acid.

Questions?

Call Method at 1-877-250-3427 or FDA at 1-800-FDA-1088

Manufactured for:
Method Pharmaceuticals, LLC
Fort Worth, Texas 76118

Rev. 04/18

Principal Display Panel

NDC 58657-120-12
Magnesium Oxide
400 mg
241.3 Elemental Magnesium
Antacid
120 Tablets